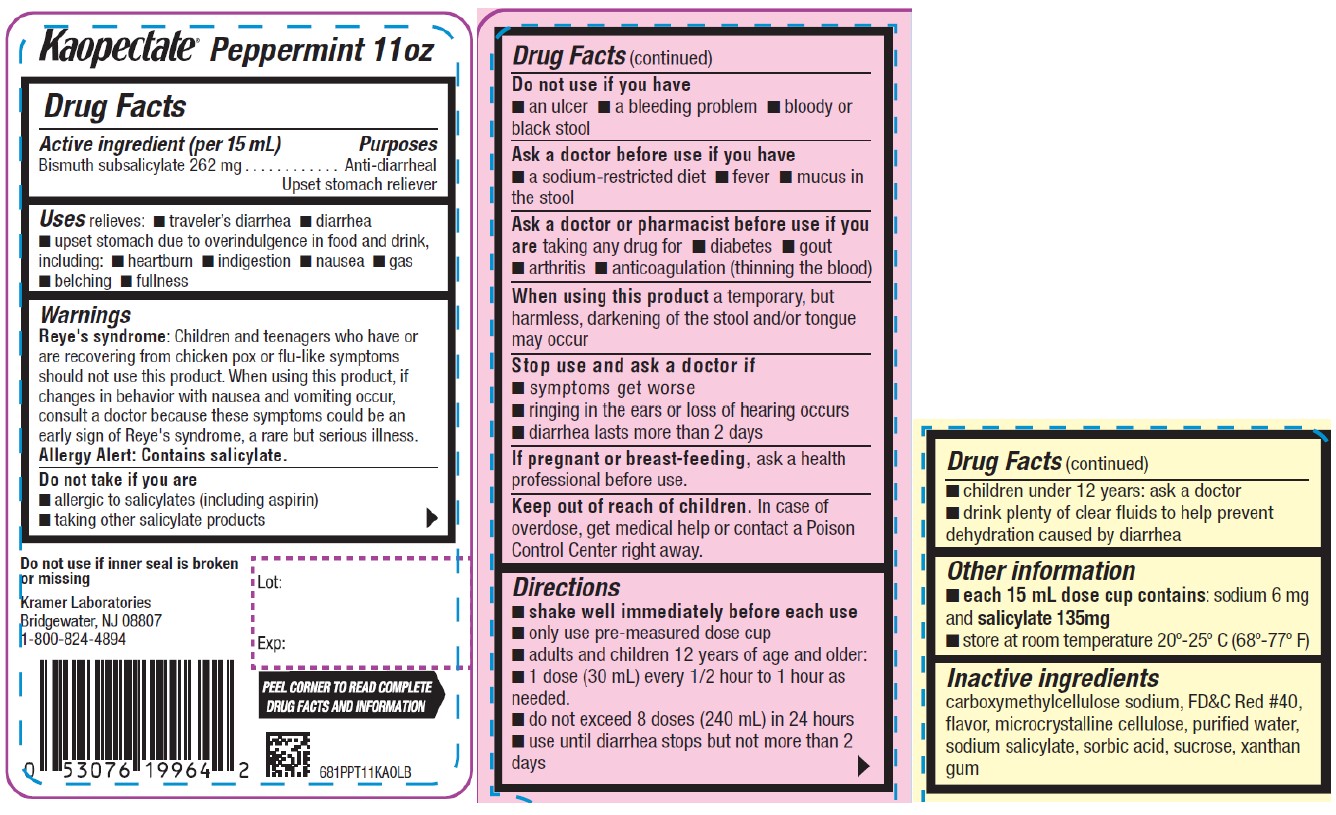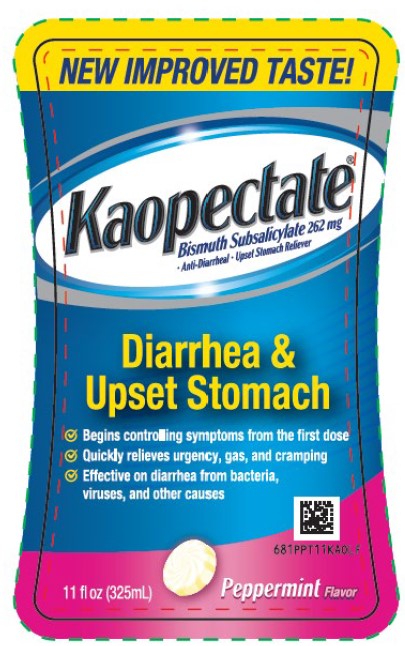 DRUG LABEL: Kaopectate Peppermint Flavor Anti Diarrheal
NDC: 55505-199 | Form: LIQUID
Manufacturer: Kramer Laboratories
Category: otc | Type: HUMAN OTC DRUG LABEL
Date: 20251219

ACTIVE INGREDIENTS: BISMUTH SUBSALICYLATE 262 mg/15 mL
INACTIVE INGREDIENTS: Carboxymethylcellulose Sodium, Unspecified; Fd&C Red No. 40; Microcrystalline Cellulose; SODIUM SALICYLATE; SORBIC ACID; SUCROSE; WATER; XANTHAN GUM

Drug Facts

ACTIVE INGREDIENT

Active ingredient (per 15 mL) | Purposes
Bismuth subsalicylate 262 mg | Anti-diarrheal Upset stomach reliever

INDICATIONS AND USAGE

Uses relieves:

- traveler’s diarrhea
- diarrhea
- upset stomach due to overindulgence in food and drink, including:
  - heartburn
  - indigestion
  - nausea
  - gas
  - belching
  - fullness

Reye's syndrome: Children and teenagers who have or are recovering from chicken pox or flu-like symptoms should not use this product. When using this product, if changes in behavior with nausea and vomiting occur, consult a doctor because these symptoms could be an early sign of Reye's syndrome, a rare but serious illness.

Do not take if you are

- allergic to salicylates (including aspirin)
- taking other salicylate products

Do not use if you have

- an ulcer
- a bleeding problem
- bloody or black stool

Ask a doctor before use if you have

- a sodium-restricted diet
- fever
- mucus in the stool

Ask a doctor or pharmacist before use if you are taking any drug for

- diabetes
- gout
- arthritis
- anticoagulation (thinning the blood)

When using this product a temporary, but harmless, darkening of the stool and/or tongue may occur

Stop use and ask a doctor if

- symptoms get worse
- ringing in the ears or loss of hearing occurs
- diarrhea lasts more than 2 days

PREGNANCY OR BREAST FEEDING

If pregnant or breast-feeding, ask a health professional before use.

Keep out of reach of children. In case of overdose, get medical help or contact a Poison Control Center right away.

Directions

- shake well immediately before each use
- only use pre-measured dose cup
- adults and children 12 years of age and older:
  - 1 dose (30 mL) every 1/2 hour to 1 hour as needed.
  - do not exceed 8 doses (240 mL) in 24 hours
  - use until diarrhea stops but not more than 2 days
- children under 12 years: ask a doctor
- drink plenty of clear fluids to help prevent dehydration caused by diarrhea

Other Information

- each 15 mL dose cup contains: sodium 6 mg and salicylate 135mg
- store at room temperature 20º-25º C (68º-77º F)

Inactive Ingredients

carboxymethylcellulose sodium, FD&C Red No. 40, flavor microcrystalline cellulose, purified water, sodium salicylate, sorbic acid, sucrose, xanthan gum

Principal Display Panel

NEW IMPROVED TASTE!
Kaopectate®
Bismuth Subsalicylate 262 MG
• Anti-Diarrheal • Upset Stomach Reliever
Diarrhea &
Upset Stomach
✓ Begins controlling symptoms from the first dose
✓ Quickly relieves urgency, gas, and cramping
✓ Effective on diarrhea from bacteria,
viruses, and other causes
11 fl oz (325mL)
Peppermint Flavor
681PPT11KA0 F

Kaopectate Peppermint 11 oz
Do not use if inner seal is broken
or missing
Kramer Laboratories
Bridgewater, NJ 08807
1-800-824-4894
Lot:
Exp:
PEEL CORNER TO READ COMPLETE
DRUG FACTS AND INFORMATION
681PPT11KA0LB